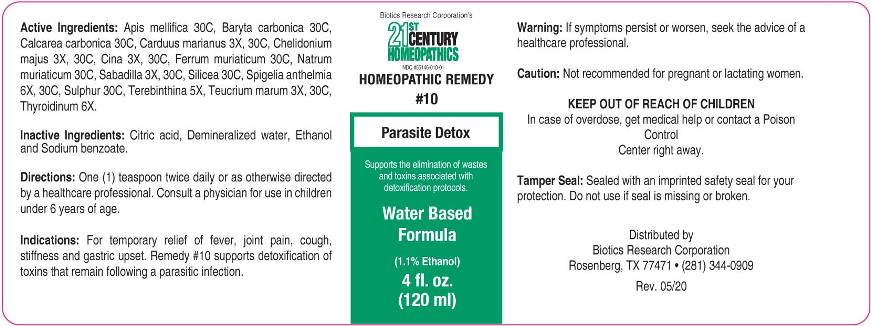 DRUG LABEL: 10 Parasite Detox
NDC: 55146-010 | Form: LIQUID
Manufacturer: Biotics Research Corporation
Category: otc | Type: HUMAN OTC DRUG LABEL
Date: 20200519

ACTIVE INGREDIENTS: MILK THISTLE 3 [hp_X]/1 mL; CHELIDONIUM MAJUS 3 [hp_X]/1 mL; ARTEMISIA CINA PRE-FLOWERING TOP 3 [hp_X]/1 mL; SCHOENOCAULON OFFICINALE SEED 3 [hp_X]/1 mL; TEUCRIUM MARUM 3 [hp_X]/1 mL; TURPENTINE OIL 5 [hp_X]/1 mL; SUS SCROFA THYROID 6 [hp_X]/1 mL; SPIGELIA ANTHELMIA 6 [hp_X]/1 mL; APIS MELLIFERA 30 [hp_C]/1 mL; BARIUM CARBONATE 30 [hp_C]/1 mL; OYSTER SHELL CALCIUM CARBONATE, CRUDE 30 [hp_C]/1 mL; FERRIC CHLORIDE HEXAHYDRATE 30 [hp_C]/1 mL; SODIUM CHLORIDE 30 [hp_C]/1 mL; SILICON DIOXIDE 30 [hp_C]/1 mL; SULFUR 30 [hp_C]/1 mL
INACTIVE INGREDIENTS: WATER; ALCOHOL; SODIUM BENZOATE; ANHYDROUS CITRIC ACID

Drug Facts:

ACTIVE INGREDIENTS:

Carduus Marianus 3X, 30C, Chelidonium Majus 3X, 30C, Cina 3X, 30C, Sabadilla 3X, 30C, Teucrium Marum 3X, 30C, Terebinthina 5X, Thyroidinum (Suis) 6X, Spigelia Anthelmia 6X, 30C, Apis Mellifica 30C, Baryta Carbonica 30C, Calcarea Carbonica 30C, Ferrum Muriaticum 30C, Natrum Muriaticum 30C, Silicea 30C, Sulphur 30C.

INDICATIONS:

For temporary relief of fever, joint pain, cough, stiffness and gastric upset. Remedy #10 supports detoxification of toxins that remain following a parasitic infection.

WARNINGS:

If symptoms persist or worsen, seek the advice of a healthcare professional.

Caution: Not recommended for pregnant or lactating women.

Keep out of reach of children. In case of overdose, get medical help or contact a Poison Control Center right away.

Tamper Seal: Sealed with an imprinted safety seal for your protection. Do not use if seal is missing or broken.

Keep out of reach of children. In case of overdose, get medical help or contact a Poison Control Center right away.

DIRECTIONS:

One (1) teaspoon twice daily or as otherwise directed by a healthcare professional. Consult a physician for use in children under 6 years of age.

INDICATIONS:

For temporary relief of fever, joint pain, cough, stiffness and gastric upset. Remedy #10 supports detoxification of toxins that remain following a parasitic infection.

INACTIVE INGREDIENTS:

Citric acid, Demineralized water, Ethanol, Sodium benzoate.

QUESTIONS:

Distributed by

Biotics Research Corporation

Rosenberg, TX 77471 • (281) 344-0909

PACKAGE LABEL DISPLAY:

Biotics Research Corporation's

21st CENTURY

HOMEOPATHICS

NDC #55146-010-01

HOMEOPATHIC REMEDY

#10

Parasite Detox

Water Based

Formula

(1.1% Ethanol)

4 fl. oz. (120ml)